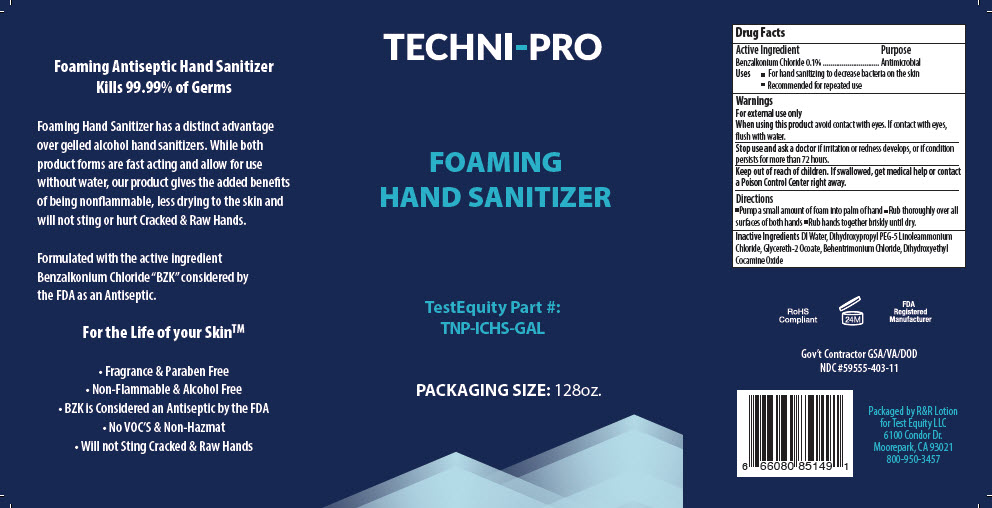 DRUG LABEL: Techni-Pro Foaming Hand Sanitizer
NDC: 59555-403 | Form: LIQUID
Manufacturer: R & R Lotion, Inc
Category: otc | Type: HUMAN OTC DRUG LABEL
Date: 20220315

ACTIVE INGREDIENTS: Benzalkonium Chloride 1 mg/1 mL
INACTIVE INGREDIENTS: WATER; Cetrimonium Chloride; Laurtrimonium Chloride; Dihydroxyethyl Cocamine Oxide; Glycereth-17 Cocoate; CITRIC ACID MONOHYDRATE

Techni-Pro Foaming Hand Sanitizer

Drug Facts

Active Ingredient

Benzalkonium Chloride 0.1%

Purpose

Antimicrobial

Uses

- For hand sanitizing to decrease bacteria on the skin
- Recommended for repeated use

Warnings

For external use only

When using this product avoid contact with eyes. If contact with eyes, flush with water.

Stop use and ask a doctor if irritation or redness develops, or if condition persists for more than 72 hours.

Keep out of reach of children. If swallowed, get medical help or contact a Poison Control Center right away.

Directions

- Pump a small amount of foam into palm of hand
- Rub thoroughly over all surfaces of both hands
- Rub hands together briskly until dry.

Inactive Ingredients

DI Water, Dihydroxypropyl PEG-5 Linoleammonium Chloride, Glycereth-2 Ocoate, Behentrimonium Chloride, Dihydroxyethyl Cocamine Oxide

PRINCIPAL DISPLAY PANEL - 3785 mL Bottle Label

TECHNI-PRO

FOAMING
HAND SANITIZER

TestEquity Part #:
TNP-ICHS-GAL

PACKAGING SIZE: 128oz.